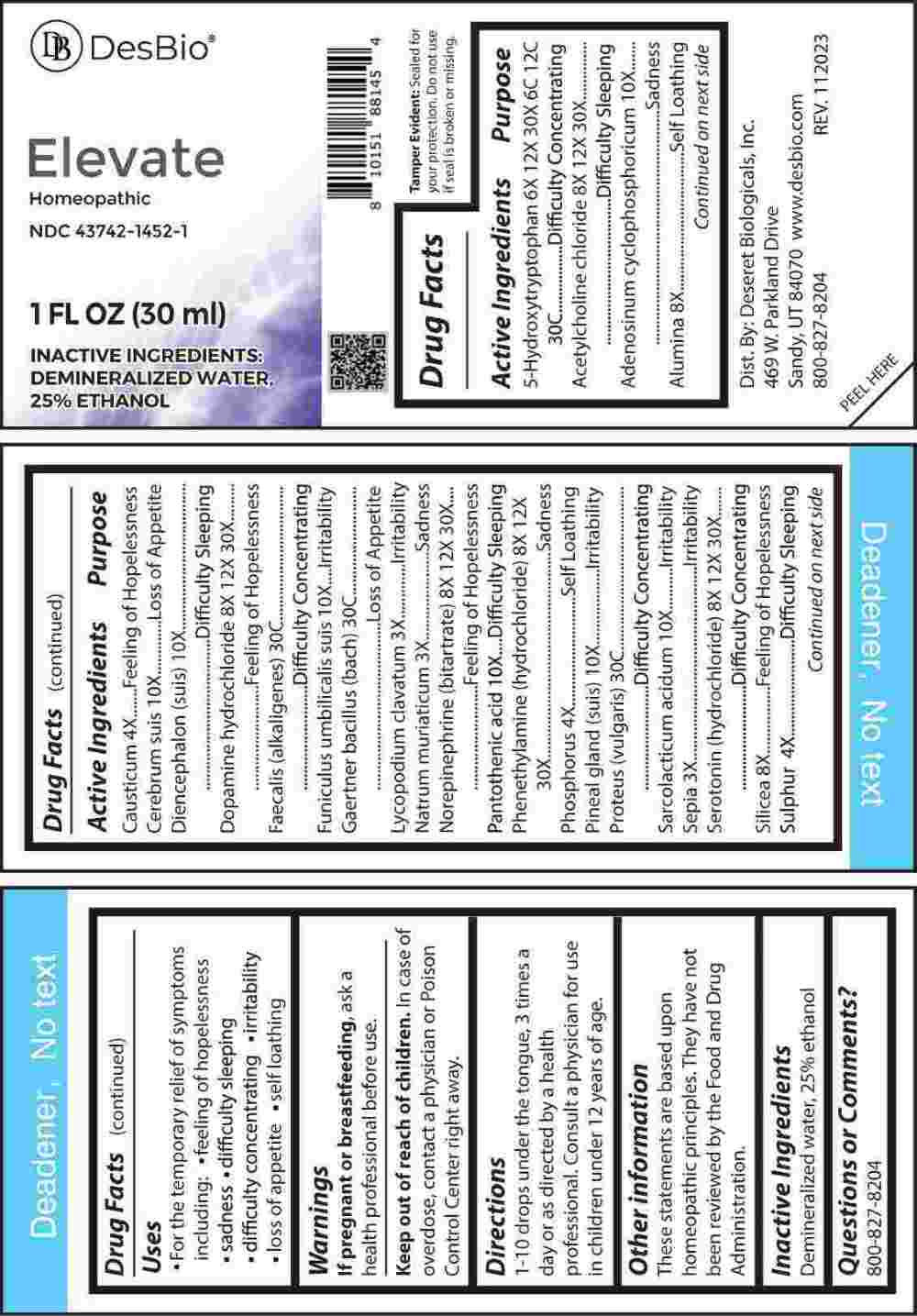 DRUG LABEL: Elevate
NDC: 43742-1452 | Form: LIQUID
Manufacturer: Deseret Biologicals, Inc.
Category: homeopathic | Type: HUMAN OTC DRUG LABEL
Date: 20240311

ACTIVE INGREDIENTS: LYCOPODIUM CLAVATUM SPORE 3 [hp_X]/1 mL; SODIUM CHLORIDE 3 [hp_X]/1 mL; SEPIA OFFICINALIS JUICE 3 [hp_X]/1 mL; CAUSTICUM 4 [hp_X]/1 mL; PHOSPHORUS 4 [hp_X]/1 mL; SULFUR 4 [hp_X]/1 mL; OXITRIPTAN 6 [hp_X]/1 mL; ALUMINUM OXIDE 8 [hp_X]/1 mL; SILICON DIOXIDE 8 [hp_X]/1 mL; ACETYLCHOLINE CHLORIDE 8 [hp_X]/1 mL; DOPAMINE HYDROCHLORIDE 8 [hp_X]/1 mL; NOREPINEPHRINE BITARTRATE 8 [hp_X]/1 mL; PHENETHYLAMINE HYDROCHLORIDE 8 [hp_X]/1 mL; SEROTONIN HYDROCHLORIDE 8 [hp_X]/1 mL; ADENOSINE CYCLIC PHOSPHATE 10 [hp_X]/1 mL; SUS SCROFA CEREBRUM 10 [hp_X]/1 mL; SUS SCROFA DIENCEPHALON 10 [hp_X]/1 mL; SUS SCROFA UMBILICAL CORD 10 [hp_X]/1 mL; PANTOTHENIC ACID 10 [hp_X]/1 mL; SUS SCROFA PINEAL GLAND 10 [hp_X]/1 mL; LACTIC ACID, L- 10 [hp_X]/1 mL; ALCALIGENES FAECALIS 30 [hp_C]/1 mL; SALMONELLA ENTERICA SUBSP. ENTERICA SEROVAR ENTERITIDIS 30 [hp_C]/1 mL; PROTEUS VULGARIS 30 [hp_C]/1 mL
INACTIVE INGREDIENTS: WATER; ALCOHOL

DRUG FACTS:

ACTIVE INGREDIENTS:

5-Hydroxytryptophan 6X, 12X, 30X, 6C, 12C, 30C, Acetylcholine Chloride 8X, 12X, 30X, Adenosinum Cyclophosphoricum 10X, Alumina 8X, Causticum 4X, Cerebrum (Suis) 10X, Diencephalon (Suis) 10X, Dopamine Hydrochloride 8X, 12X, 30X, Faecalis (Alkaligenes) 30C, Funiculus Umbilicalis Suis 10X, Gaertner Bacillus (Bach) 30C, Lycopodium Clavatum 3X, Natrum Muriaticum 3X, Norepinephrine (Bitartrate) 8X, 12X, 30X, Pantothenic Acid 10X, Phenylethylamine (Hydrochloride) 8X, 12X, 30X, Phosphorus 4X, Pineal Gland (Suis) 10X, Proteus (Vulgaris) 30C, Sarcolacticum Acidum 10X, Sepia 3X, Serotonin (Hydrochloride) 8X, 12X, 30X, Silicea 8X, Sulphur 4X.

PURPOSE:

5-Hydroxytryptophan – Difficulty Concentrating, Acetylcholine Chloride-Difficulty Sleeping, Adenosinum Cyclophosphoricum - Sadness, Alumina – Self Loathing, Causticum – Feeling of Helplessness, Cerebrum (Suis) – Loss of Appetite, Diencephalon (Suis) – Difficulty Sleeping, Dopamine Hydrochloride – Feeling of Hopelessness, Faecalis (Alkaligenes) – Difficulty Concentrating, Funiculus Umbilicalis Suis - Irritability, Gaertner Bacillus (Bach) – Loss of Appetite, Lycopodium Clavatum - Irritability, Natrum Muriaticum - Sadness, Norepinephrine (Bitartrate) – Feeling of Hopelessness, Pantothenic Acid – Difficulty Sleeping, Phenylethylamine (Hydrochloride) -Sadness, Phosphorus – Self Loathing, Pineal Gland (Suis) - Irritability, Proteus (Vulgaris) – Difficulty Concentrating, Sarcolacticum Acidum - Irritability, Sepia - Irritability, Serotonin (Hydrochloride) – Difficulty Concentrating, Silicea – Feeling of Hopelessness, Sulphur – Difficulty Sleeping

USES:

• For the temporary relief of symptoms including:

• feelings of helplessness • sadness • difficulty sleeping

• difficulty concentrating • irritability • loss of appetite • self loathing

These statements are based upon homeopathic principles. They have not been reviewed by the Food and Drug Administration.

WARNINGS:

If pregnant or breast-feeding, ask a health professional before use.

Keep out of reach of children. In case of overdose, contact a physician or Poison Control Center right away.

Tamper Evident: Sealed for your protection.

Do not use if seal is broken or missing.

KEEP OUT OF REACH OF CHILDREN:

In case of overdose, contact a physician or Poison Control Center right away.

DIRECTIONS:

1-10 drops under the tongue, 3 times a day or as directed by a health professional. Consult a physician for use in children under 12 years of age.

INACTIVE INGREDIENTS:

Demineralized water, 25% ethanol

QUESTIONS:

Dist. By: Deseret Biologicals, Inc.

469 W. Parkland Drive

Sandy, UT 84070

www.desbio.com

800-827-8204

PACKAGE LABEL DISPLAY:

Des Bio

Elevate

Homeopathic
NDC 43742-1452-1
1 FL OZ (30 ml)